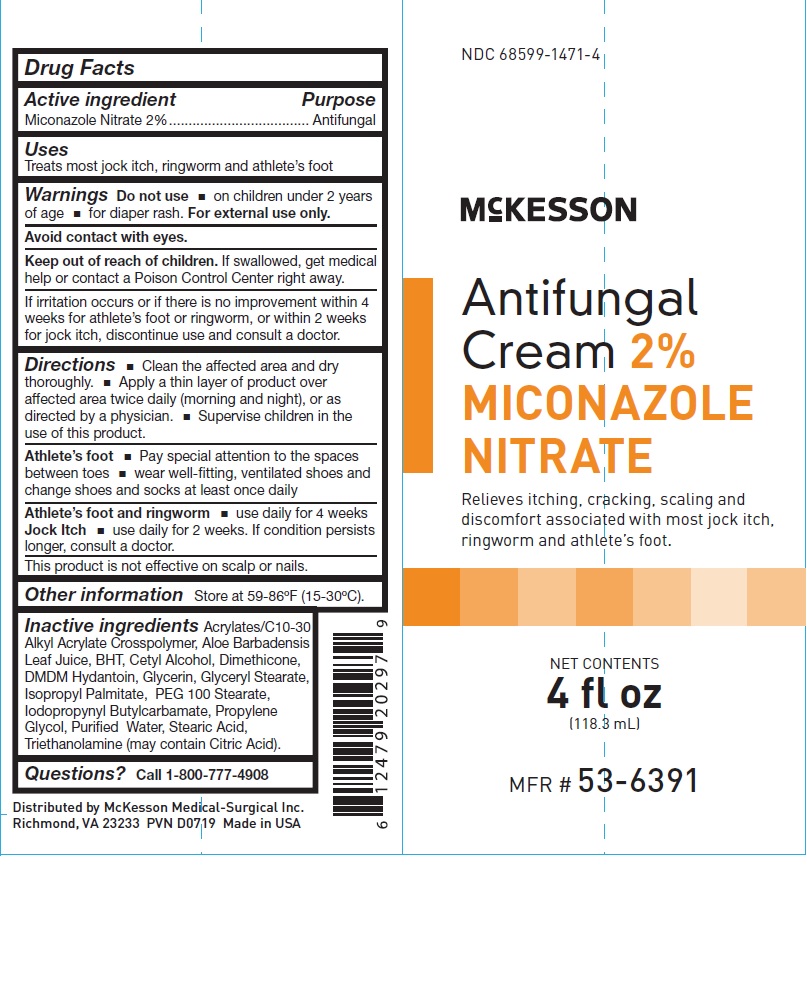 DRUG LABEL: Miconazole Nitrate
NDC: 68599-1471 | Form: CREAM
Manufacturer: McKesson
Category: otc | Type: HUMAN OTC DRUG LABEL
Date: 20241010

ACTIVE INGREDIENTS: MICONAZOLE NITRATE 2 mg/100 mg
INACTIVE INGREDIENTS: DMDM HYDANTOIN; GLYCERYL MONOSTEARATE; ISOPROPYL PALMITATE; PEG-100 STEARATE; STEARIC ACID; ALOE VERA LEAF; PROPYLENE GLYCOL; CARBOMER COPOLYMER TYPE A (ALLYL PENTAERYTHRITOL CROSSLINKED); BUTYLATED HYDROXYTOLUENE; CETYL ALCOHOL; GLYCERIN; WATER; DIMETHICONE; TROLAMINE; IODOPROPYNYL BUTYLCARBAMATE

Antifungal

Drug Facts

Active ingredient

Miconazole Nitrate 2%

Purpose

Antifungal

Uses

Treats most jock itch, ringworm and athlete’s foot

Warnings

Do not use

- on children under 2 years of age
- for diaper rash.

For external use only.

Avoid contact with eyes.

STOP USE

Consult a Doctor

If irritation occurs or if there is no improvement within 4 weeks for athlete’s foot or ringworm,

or within 2 weeks for jock itch.

Keep out of reach of children.
If swallowed, get medical help or contact a Poison Control Center right away.

Directions

- Clean the affected area and dry thoroughly.
- Apply a thin layer of product over affected area twice daily (morning and night), or as directed by a physician.
- Supervise children in the use of this product.

Athlete’s foot

- Pay special attention to the spaces between toes
- wear well-fitting, ventilated shoes and change shoes and socks at least once daily

Athlete’s foot and ringworm

- use daily for 4 weeks

Jock Itch

- use daily for 2 weeks.

If condition persists longer, consult a doctor.

Other Information

- This product is not effective on scalp or nails.
- Store at 59-86ºF (15-30ºC).

Inactive ingredients

Acrylates/C10-30 Alkyl Acrylate Crosspolymer, Aloe Barbadensis Leaf Juice, BHT, Cetyl Alcohol, Dimethicone,
DMDM Hydantoin, Glycerin, Glyceryl Stearate, Isopropyl Palmitate, PEG 100 Stearate,Iodopropynyl Butylcarbamate,

Propylene Glycol, Purified Water, Stearic Acid, Triethanolamine (may contain Citric Acid).

PACKAGE LABEL

NDC 68599-1471-4

McKesson
Antifungal Cream 2%
MICONAZOLE
NITRATE

Relieves itching, cracking, scaling and
discomfort associated with most jock itch,
ringworm and athlete’s foot.

4 fl oz
(118.3 mL)

MFR # 53-6391